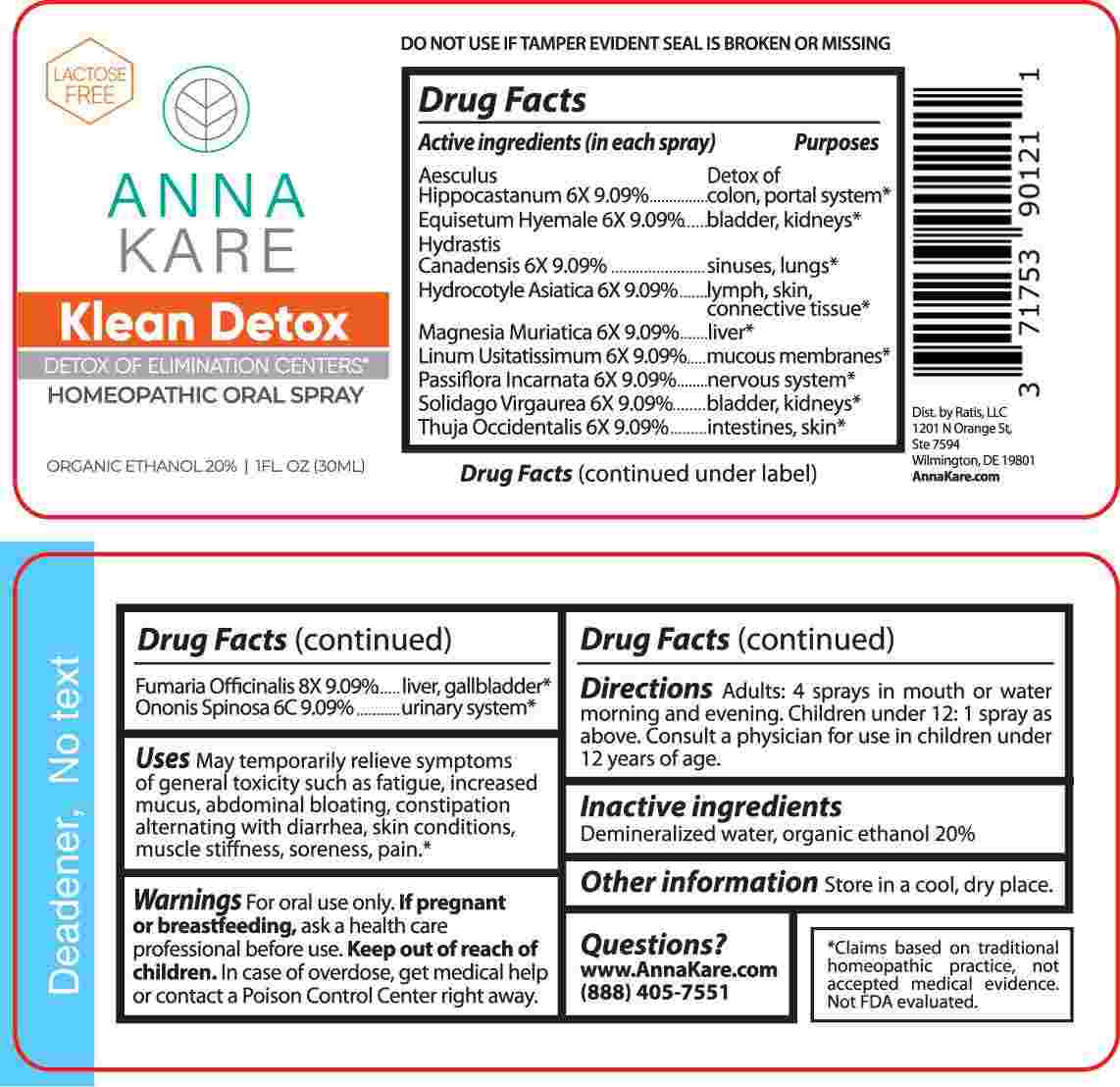 DRUG LABEL: Klean Detox
NDC: 71753-9012 | Form: SPRAY
Manufacturer: Ratis, LLC
Category: homeopathic | Type: HUMAN OTC DRUG LABEL
Date: 20241108

ACTIVE INGREDIENTS: HORSE CHESTNUT 6 [hp_X]/1 mL; EQUISETUM HYEMALE WHOLE 6 [hp_X]/1 mL; GOLDENSEAL 6 [hp_X]/1 mL; CENTELLA ASIATICA WHOLE 6 [hp_X]/1 mL; FLAX SEED 6 [hp_X]/1 mL; MAGNESIUM CHLORIDE 6 [hp_X]/1 mL; PASSIFLORA INCARNATA FLOWERING TOP 6 [hp_X]/1 mL; SOLIDAGO VIRGAUREA FLOWERING TOP 6 [hp_X]/1 mL; THUJA OCCIDENTALIS LEAFY TWIG 6 [hp_X]/1 mL; FUMARIA OFFICINALIS FLOWERING TOP 8 [hp_X]/1 mL; ONONIS SPINOSA WHOLE 6 [hp_C]/1 mL
INACTIVE INGREDIENTS: WATER; ALCOHOL

DRUG FACTS:

ACTIVE INGREDIENT:

(in each spray) Aesculus Hippocastanum 6X 9.09%, Equisetum Hyemale 6X 9.09%, Hydrastis Canadensis 6X 9.09%, Hydrocotyle Asiatica 6X 9.09%, Linum Usitatissimum 6X 9.09%, Magnesia Muriatica 6X 9.09%, Passiflora Incarnata 6X 9.09%, Solidago Virgaurea 6X 9.09%, Thuja Occidentalis 6X 9.09%, Fumaria Officinalis 8X 9.09%, Ononis Spinosa 6C 9.09%.

PURPOSE:

Aesculus Hippocastanum – Detox of colon, portal system,* Equisetum Hyemale – bladder, kidneys,* Hydrastis Canadensis – sinuses, lungs,* Hydrocotyle Asiatica – lymph, skin, connective tissue,** Linum Usitatissimum – mucous membranes,* Magnesia Muriatica - liver,* Passiflora Incarnata – nervous system,* Solidago Virgaurea – bladder, kidneys,* Thuja Occidentalis – intestines, skin,* Fumaria Officinalis – liver, gallbladder,* Ononis Spinosa – urinary system*

*Claims based on traditional homeopathic practice, not accepted medical evidence. Not FDA evaluated.

USES:

May temporarily relieve symptoms of general toxicity such as fatigue, increased mucus, abdominal bloating, constipation alternating with diarrhea, skin conditions, muscle stiffness, soreness, pain.*

*Claims based on traditional homeopathic practice, not accepted medical evidence. Not FDA evaluated.

WARNINGS:

For oral use only.

If pregnant or breast-feeding, ask a health care professional before use.

Keep out of reach of children. In case of overdose, get medical help or contact a Poison Control Center right away.

DO NOT USE IF TAMPER EVIDENT SEAL IS BROKEN OR MISSING

KEEP OUT OF REACH OF CHILDREN:

In case of overdose, get medical help or contact a Poison Control Center right away.

DIRECTIONS:

Adults: 4 sprays in mouth or water morning and evening.

Children under 12: 1 spray as above

Consult a physician for use in children under 12 years of age.

Store in a cool, dry place.

INACTIVE INGREDIENTS:

Demineralized water, organic ethanol 20%

QUESTIONS:

Dist. by Ratis, LLC

1201 N Orange St,

Ste 7594

Wilmington, DE 19801

AnnaKare.com

(888) 405-7551

PACKAGE LABEL DISPLAY:

LACTOSE FREE

ANNA KARE

Klean Detox

DETOX OF ELIMINATION CENTERS

HOMEOPATHIC ORAL SPRAY

1FL OZ (30ML)